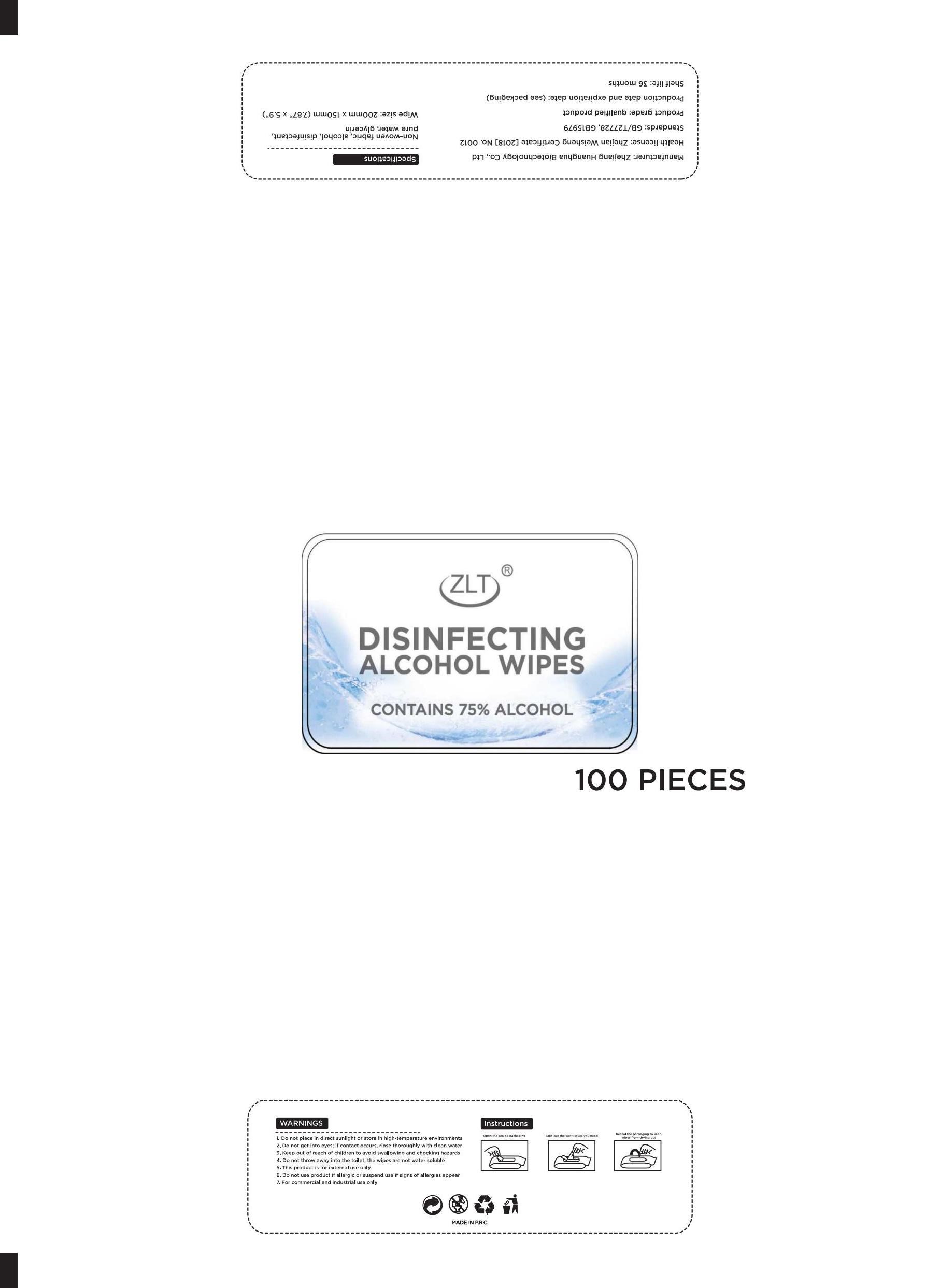 DRUG LABEL: DISINFECTING ALCOHOL WIPES
NDC: 41546-023 | Form: CLOTH
Manufacturer: Zhejiang Huanghua Biological Technology Co., Ltd
Category: otc | Type: HUMAN OTC DRUG LABEL
Date: 20201222

ACTIVE INGREDIENTS: ALCOHOL 75 g/100 g; BENZALKONIUM CHLORIDE 0.65 g/100 g; METHYLISOTHIAZOLINONE 0.65 g/100 g; PROPYLENE GLYCOL 0.65 g/100 g; PHENOXYETHANOL 0.65 g/100 g
INACTIVE INGREDIENTS: WATER

DOSAGE AND ADMINISTRATION

Please do not place in direct sunlight or in a place with high temperature

INACTIVE INGREDIENT

pure water

INDICATIONS AND USAGE

1.Open the box and seal it

2.Take out all the wet tissues you need
3.Close the box seal

ACTIVE INGREDIENT

alcohol

Benzalkamine

2-methyl-4-isothiazoline-3-one

propylene glyco

2-phenoxyethanol

keep out of reach of children

PURPOSE

Disinfection
Sterilization
No Rinseing

WARNINGS

1 Do not place in direct sunlight or store in high-temperature environments
2. Do not get into eyes; If contact occurs, rinse thoroughly with clean water
3. Keep out of reach of children to avoid swal lowing and chocking hazards
4. Do not throw away into the toilet; the wipes are not water soluble
5. This product is for externaluse only
6. Do not use product if allergic or suspend use if signs of allergies appear
7. For commercial and industrial use only